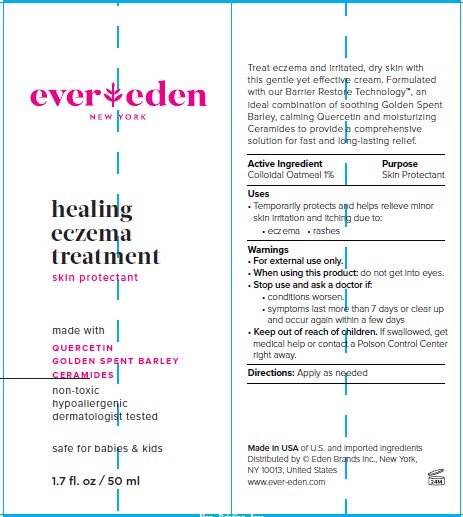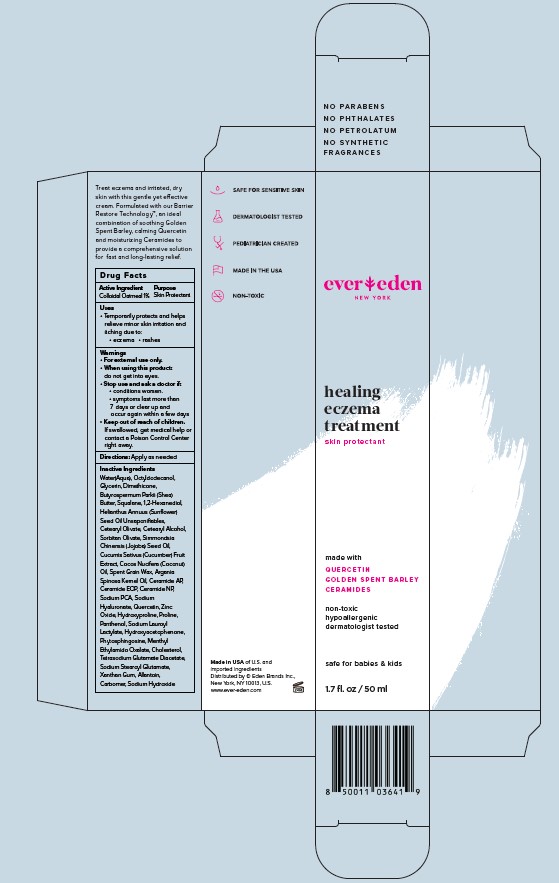 DRUG LABEL: Evereden Healing Eczema Treatment
NDC: 72113-106 | Form: CREAM
Manufacturer: Eden Brands, Inc.
Category: otc | Type: HUMAN OTC DRUG LABEL
Date: 20241213

ACTIVE INGREDIENTS: OATMEAL 1 g/100 mL
INACTIVE INGREDIENTS: OCTYLDODECANOL; SQUALANE; SORBITAN OLIVATE; CUCUMIS SATIVUS WHOLE; ARGANIA SPINOSA SEED; DIMETHICONE; BUTYROSPERMUM PARKII (SHEA) BUTTER UNSAPONIFIABLES; 1,2-HEXANEDIOL; HELIANTHUS ANNUUS SEED WAX; COCOS NUCIFERA WHOLE; SIMMONDSIA CHINENSIS SEED; CERAMIDE AP; TETRASODIUM GLUTAMATE DIACETATE; ARGAN OIL; SODIUM PYRROLIDONE CARBOXYLATE; ALLANTOIN; CARBOMER HOMOPOLYMER, UNSPECIFIED TYPE; CETEARYL OLIVATE; GLYCERIN; CERAMIDE NP; ZINC OXIDE; PHYTOSPHINGOSINE; CHOLESTEROL; SODIUM HYDROXIDE; CETOSTEARYL ALCOHOL; CERAMIDE 1; HYALURONATE SODIUM; QUERCETIN; HYDROXYPROLINE; PROLINE; PANTHENOL; SODIUM LAUROYL LACTYLATE; HYDROXYACETOPHENONE; MENTHYL ETHYLAMIDO OXALATE; SODIUM STEAROYL GLUTAMATE; XANTHAN GUM

Evereden Healing Eczema Treatment

ACTIVE INGREDIENT

Colloidal Oatmeal 1%

PURPOSE

Skin Protectant

USES

Temporarily protects and helps relieve minor skin irritation and itching due to: • eczema • rashes

WARNINGS

- For external use only.
- When using this product: Do not get into eyes.
- Stop use and ask a doctor if: - conditions worsen. - symptoms last more than 7 days or clear up and occur again within a few days.

WARNINGS

• Keep out of reach of children. If swallowed, get medical help or contact a Poison Control Center right away.

DIRECTIONS

Apply as needed

INACTIVE INGREDIENTS

Water(Aqua), Octyldodecanol, Glycerin, Dimethicone, Butyrospermum Parkii (Shea) Butter, Squalane, 1,2-Hexanediol, Helianthus Annuus (Sunflower) Seed Oil Unsaponifiables, Cetearyl Olivate, Cetearyl Alcohol, Sorbitan Olivate, Simmondsia Chinensis (Jojoba) Seed Oil, Cucumis Sativus (Cucumber) Fruit Extract, Cocos Nucifera (Coconut) Oil, Spent Grain Wax, Argania Spinosa Kernel Oil, Ceramide AP, Ceramide EOP, Ceramide NP, Sodium PCA, Sodium Hyaluronate, Quercetin, Zinc Oxide, Hydroxyproline, Proline, Panthenol, Sodium Lauroyl Lactylate, Hydroxyacetophenone, Phytosphingosine, Menthyl Ethylamido Oxalate, Cholesterol, Tetrasodium Glutamate Diacetate, Sodium Stearoyl Glutamate, Xanthan Gum, Allantoin, Carbomer, Sodium Hydroxide